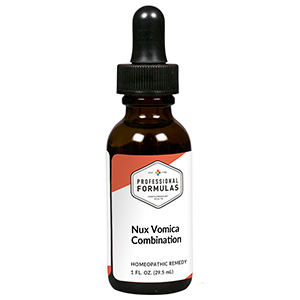 DRUG LABEL: Nux Vomica Combination
NDC: 63083-9235 | Form: LIQUID
Manufacturer: Professional Complementary Health Formulas
Category: homeopathic | Type: HUMAN OTC DRUG LABEL
Date: 20190815

ACTIVE INGREDIENTS: BRYONIA ALBA ROOT 3 [hp_X]/29.5 mL; LYCOPODIUM CLAVATUM SPORE 3 [hp_X]/29.5 mL; STRYCHNOS NUX-VOMICA SEED 3 [hp_X]/29.5 mL; CITRULLUS COLOCYNTHIS FRUIT PULP 6 [hp_X]/29.5 mL; SULFUR 10 [hp_X]/29.5 mL
INACTIVE INGREDIENTS: ALCOHOL; WATER

R235

ACTIVE INGREDIENTS

Bryonia 3X, 6X, 10X, 15X, 30X, 200X, 1000X
Lycopodium clavatum 3X, 10X, 30X, 200X, 1000X
Nux vomica 3X, 10X, 15X, 30X, 200X, 1000X
Colocynthis 6X, 10X, 30X, 200X
Sulphur 10X, 30X, 200X

QUESTIONS

Professional Formulas

PO Box 2034 Lake Oswego, OR 97035

INDICATIONS

For the temporary relief of nausea, constipation, indigestion, heartburn, or irritability, especially after consumption of alcohol, caffeine, or nicotine.*

PURPOSE

*Claims based on traditional homeopathic practice, not accepted medical evidence. Not FDA evaluated.

WARNINGS

In case of overdose, get medical help or contact a poison control center right away.

Keep out of the reach of children.

PREGNANCY OR BREAST FEEDING

If pregnant or breastfeeding, ask a healthcare professional before use.

DIRECTIONS

Place drops under tongue 30 minutes before/after meals. Adults and children 12 years and over: Take 10 drops up to 3 times per day. Consult a physician for use in children under 12 years of age.

OTHER INFORMATION

Tamper resistant. If seal is broken, do not use. After opening, close container tightly and store at room temperature away from heat.

INACTIVE INGREDIENTS

40% ethanol, purified water.

LABEL

Est 1985

Professional Formulas

Complementary Health

Nux Vomica Combination

Homeopathic Remedy

1 FL. OZ. (29.5 mL)